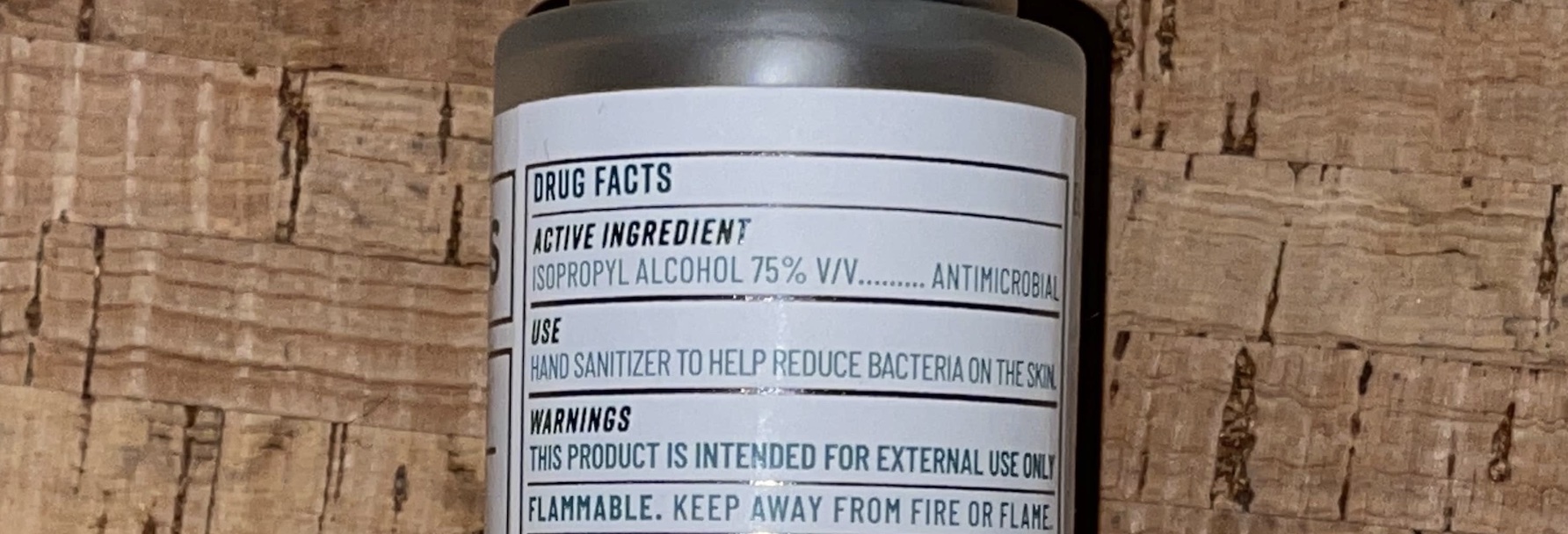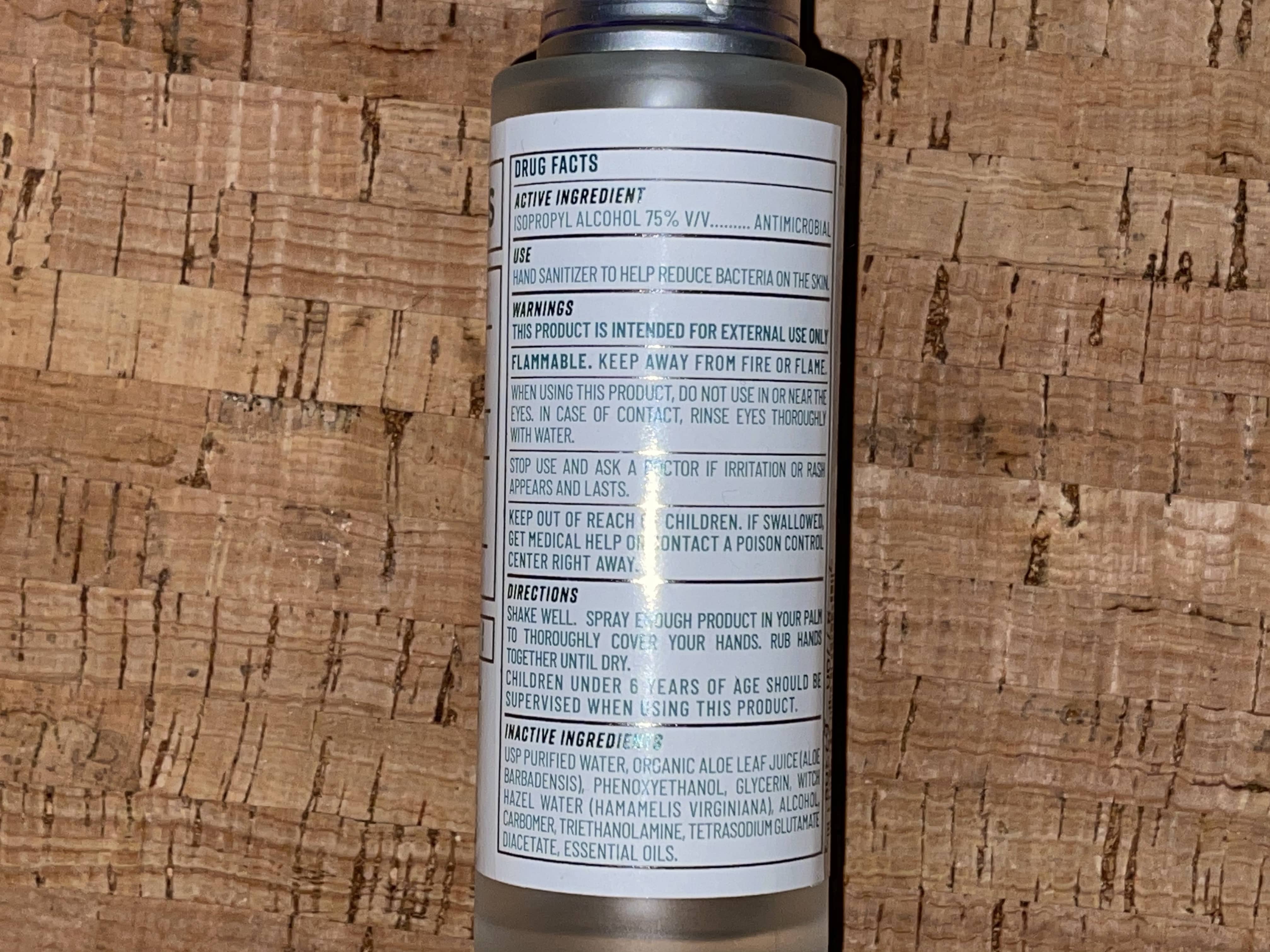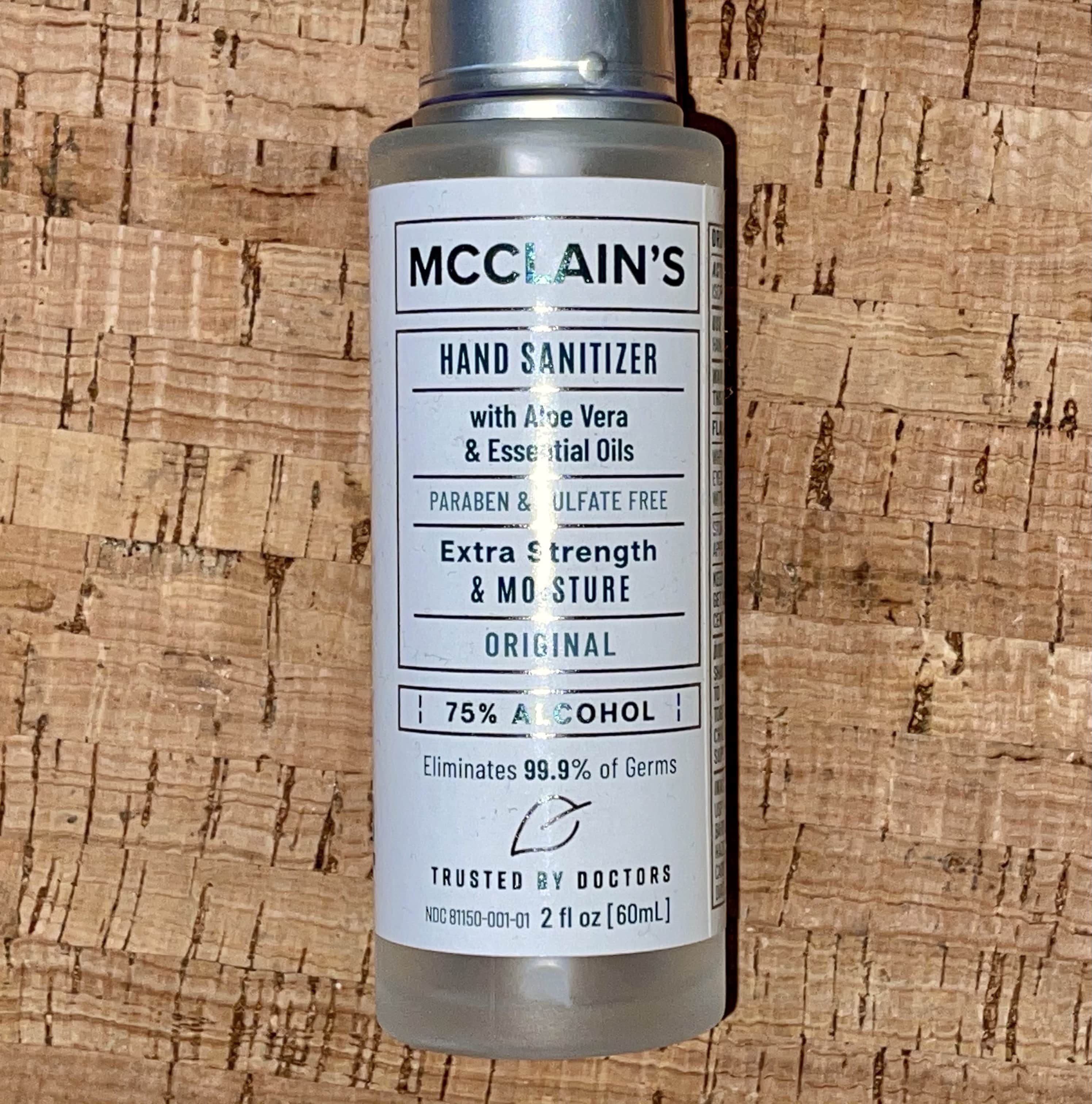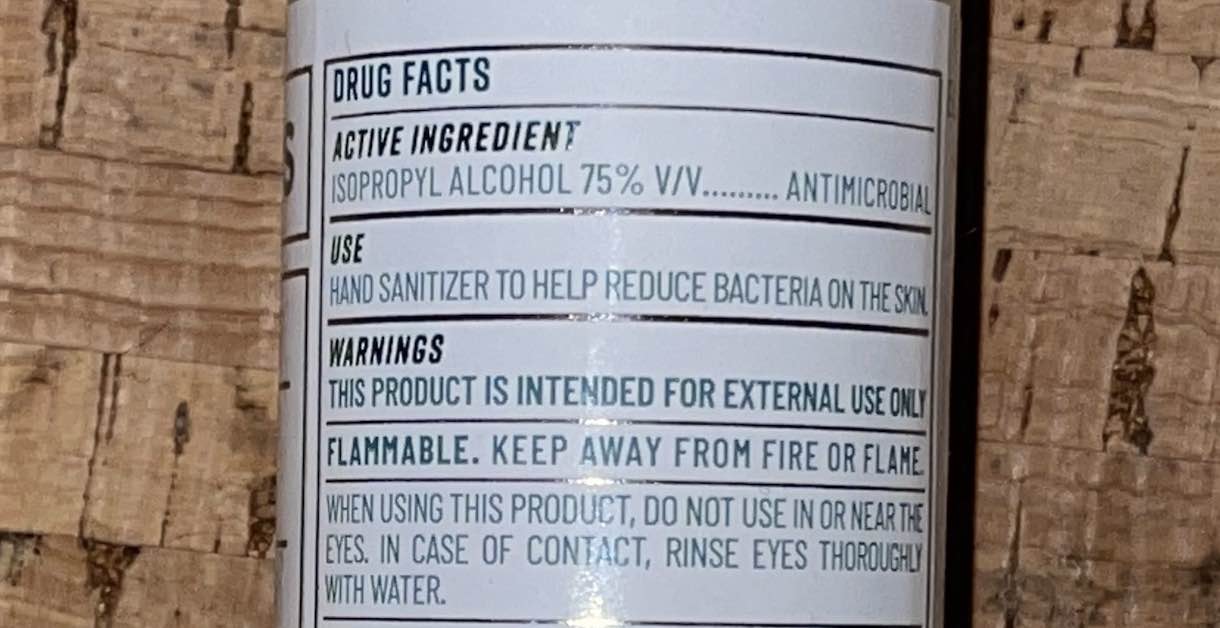 DRUG LABEL: McClains Extra Strength And Moisture Hand Sanitizer Original
NDC: 81150-001 | Form: LIQUID
Manufacturer: McClain's Health LLC
Category: otc | Type: HUMAN OTC DRUG LABEL
Date: 20201119

ACTIVE INGREDIENTS: ISOPROPYL ALCOHOL 75 mL/100 mL
INACTIVE INGREDIENTS: LEMON OIL; TETRASODIUM GLUTAMATE DIACETATE; CINNAMON OIL; ROSEMARY OIL; EUCALYPTUS OIL; GLYCERIN 1.25 mL/100 mL; ALOE VERA LEAF 23 mL/100 mL; WATER; WITCH HAZEL 0.25 mL/100 mL; CARBOMER 940; CLOVE OIL; PHENOXYETHANOL 0.25 mL/100 mL; ALCOHOL 0.25 mL/100 mL

Hand sanitizer

The hand sanitizer is manufactured using only the following United States Pharmacopoeia (USP) grade ingredients in the preparation of the product (percentage in final product formulation) consistent with CDC recommendations:

1. Isopropyl Alcohol (75%, v/v) in an aqueous solution denatured according to Alcohol and Tobacco Tax and Trade Bureau regulations in 27 CFR part 20.
2. Glycerol (1.45% v/v).
3. Sterile distilled water or boiled cold water.

Formulation:

Active Ingredient(s)

Isopropyl Alcohol 75% v/v. Purpose: Antiseptic

Purpose

Antiseptic, Hand Sanitizer

Use

Hand Sanitizer to help reduce bacteria on the skin.

Warnings

For external use only. Flammable. Keep away from heat or flame

Do not use

- keep out of reach of children
- do not use in or near the eyes

When using this product keep out of eyes, ears, and mouth. In case of contact with eyes, rinse eyes thoroughly with water.
Stop use and ask a doctor if irritation or rash occurs. These may be signs of a serious condition.
Keep out of reach of children. If swallowed, get medical help or contact a Poison Control Center right away.

Stop use and ask a doctor if irritation or rash occurs. These may be signs of a serious condition.

Keep out of reach of children. If swallowed, get medical help or contact a Poison Control Center right away.

Directions

- Place enough product on hands to cover all surfaces. Rub hands together until dry.

Other information

- Store between 15-30C (59-86F)
- Avoid freezing and excessive heat above 40C (104F)

Inactive ingredients

USP Purified Water, Organic Aloe Leaf Juice, Phenoxyethanol, Glycerin, Withc Hazel Water, Alcohol, Carbomer, Triethanolamine, Tetrasodium Glutamate Diacetate, Essential Oils.

RECENT MAJOR CHANGES

- Changed usage to reflect exact wording on label.

- Added image of instructions to Dosage form

Package Label - Principal Display Panel

60 ml NDC: 81150-001-01